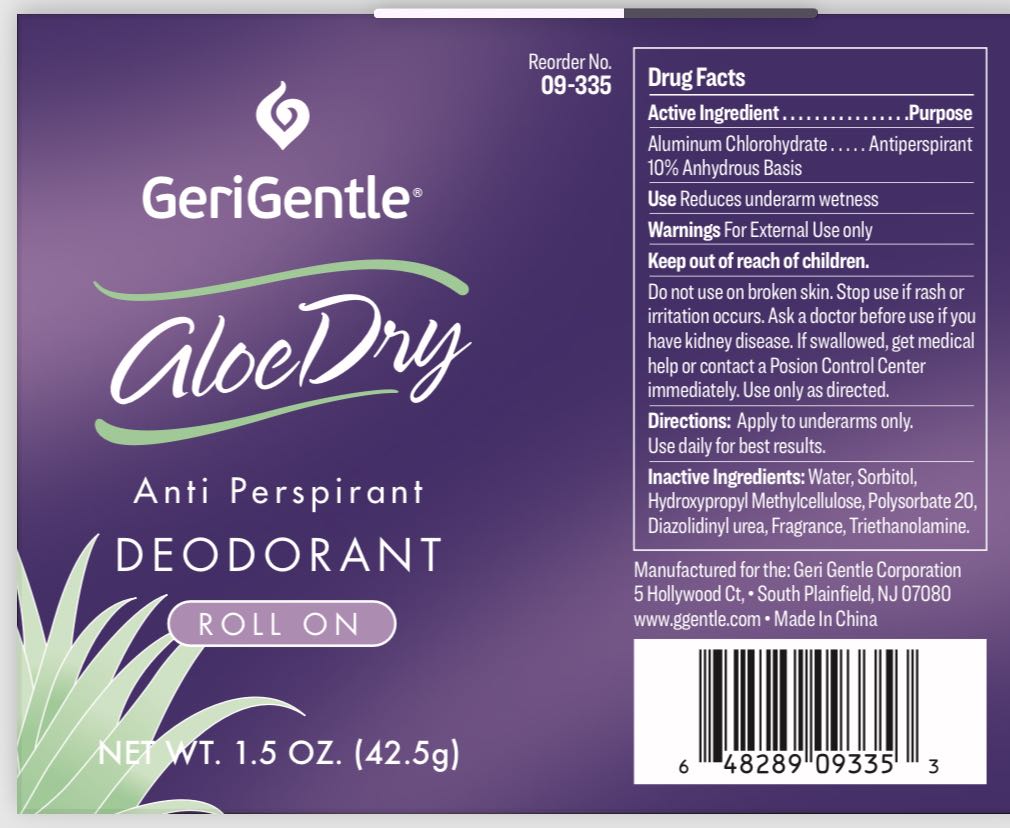 DRUG LABEL: GeriGentle Aloe Dry Anti Perspirant Deodorant Roll On
NDC: 77573-014 | Form: LIQUID
Manufacturer: Jiangsu Aimeili Cosmetic Co., Ltd.
Category: otc | Type: HUMAN OTC DRUG LABEL
Date: 20240105

ACTIVE INGREDIENTS: ALUMINUM CHLOROHYDRATE 0.1 g/1 g
INACTIVE INGREDIENTS: DIAZOLIDINYL UREA; TROLAMINE; SORBITOL; WATER; POLYSORBATE 20

77573-014

Active Ingredient

Aluminum Chlorohydrate: 10%

Purpose: Anti perspirant

INDICATIONS AND USAGE

Uses Reduces underarm wetness

Warnings

For external use only

Do not use on broken skin. Ask a doctor before use if you have kidney disease

Stop use if rash or irritation develops

Keep out of reach of children. If swallowed, get medical help or contact a Poison Control Center right away. Use only as directed.

Directions

Apply to underarm only. Use daily for best results.

Inactive Ingredient

Water, Sorbitol, Hydroxypropyl methylcellulose, Polysorbate 20, Diazolidinyl urea, Fragrance, Triethanolamine